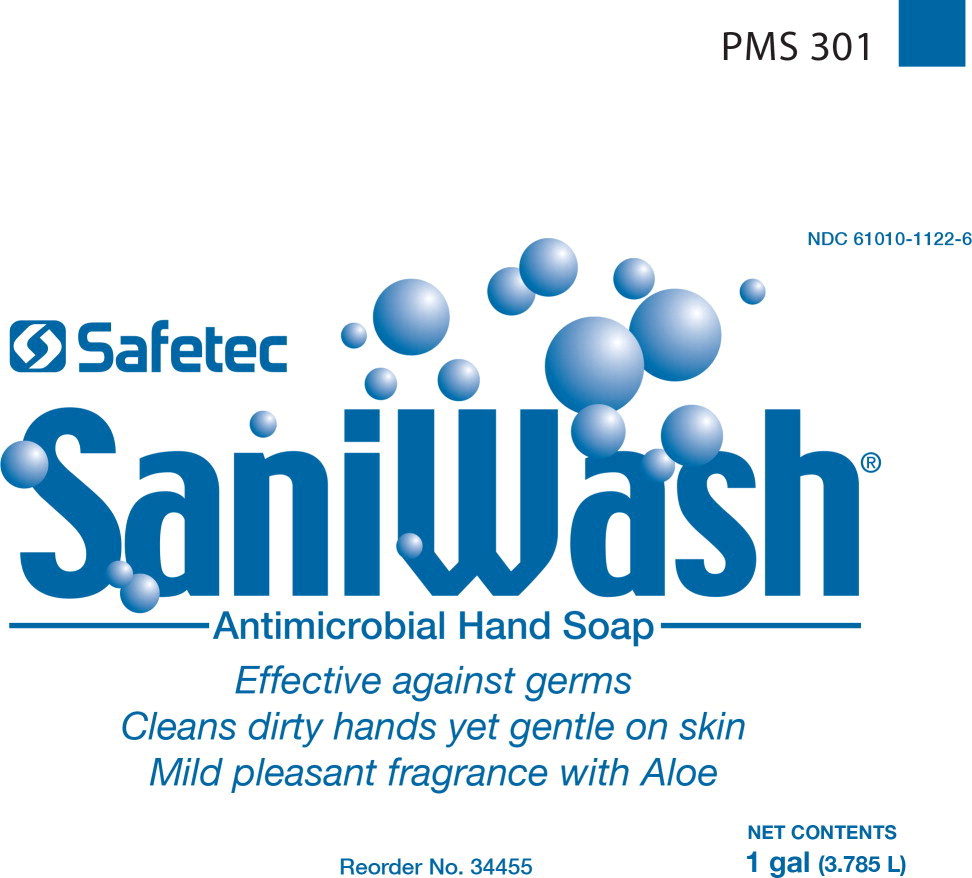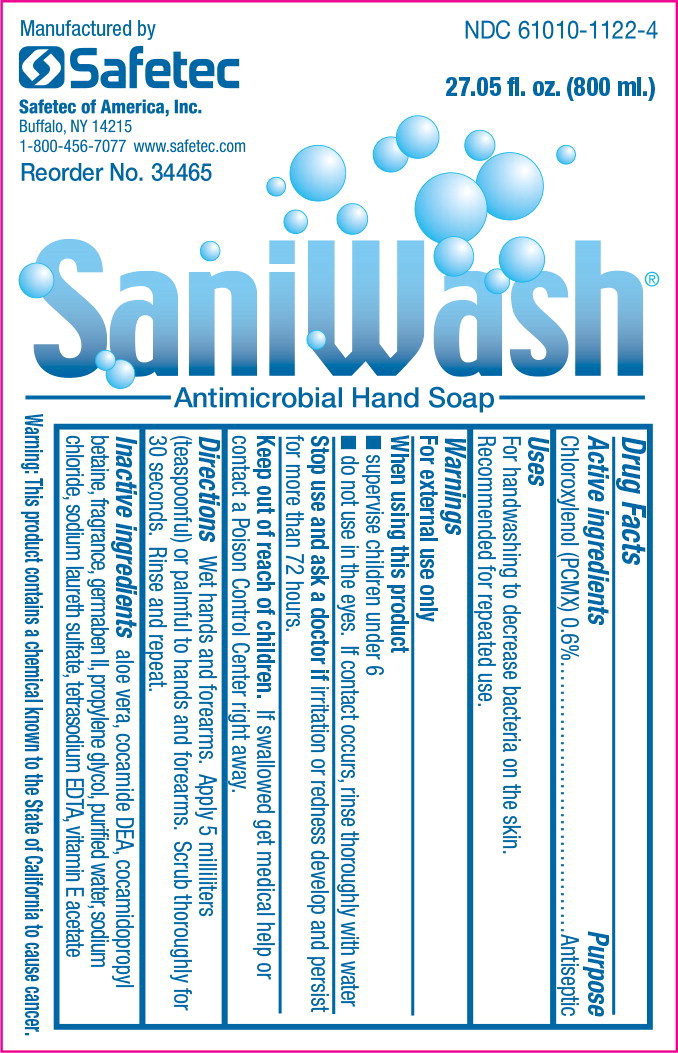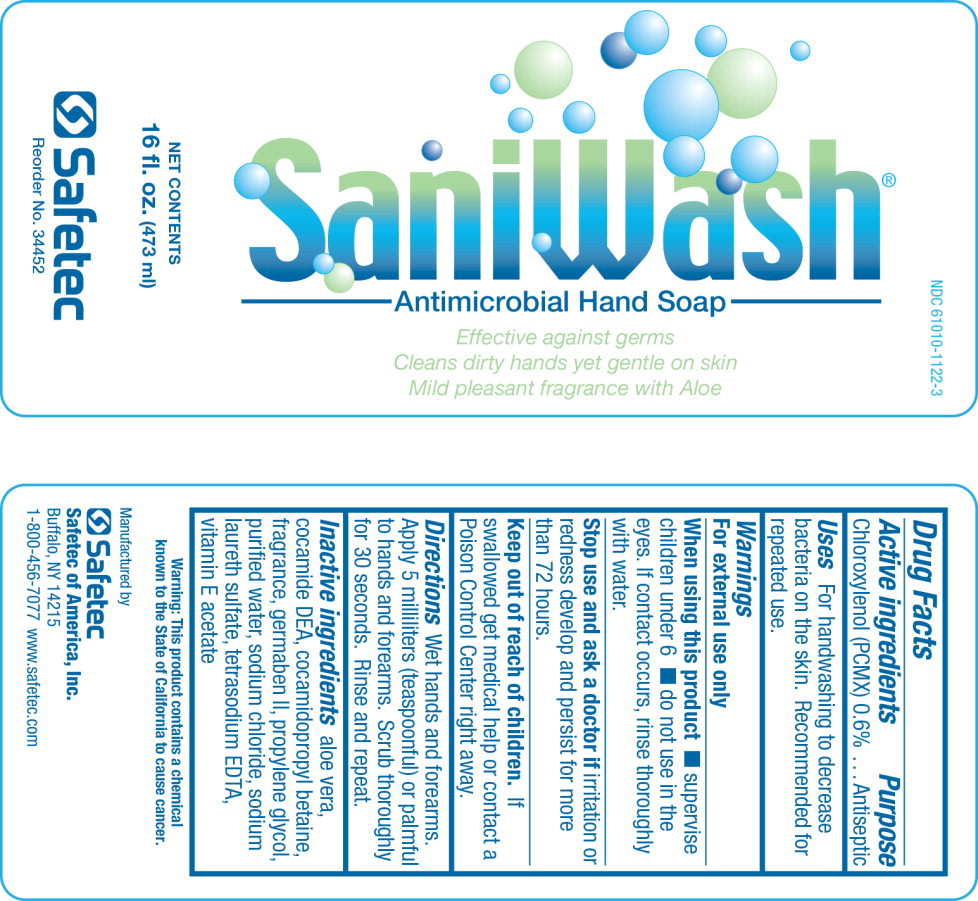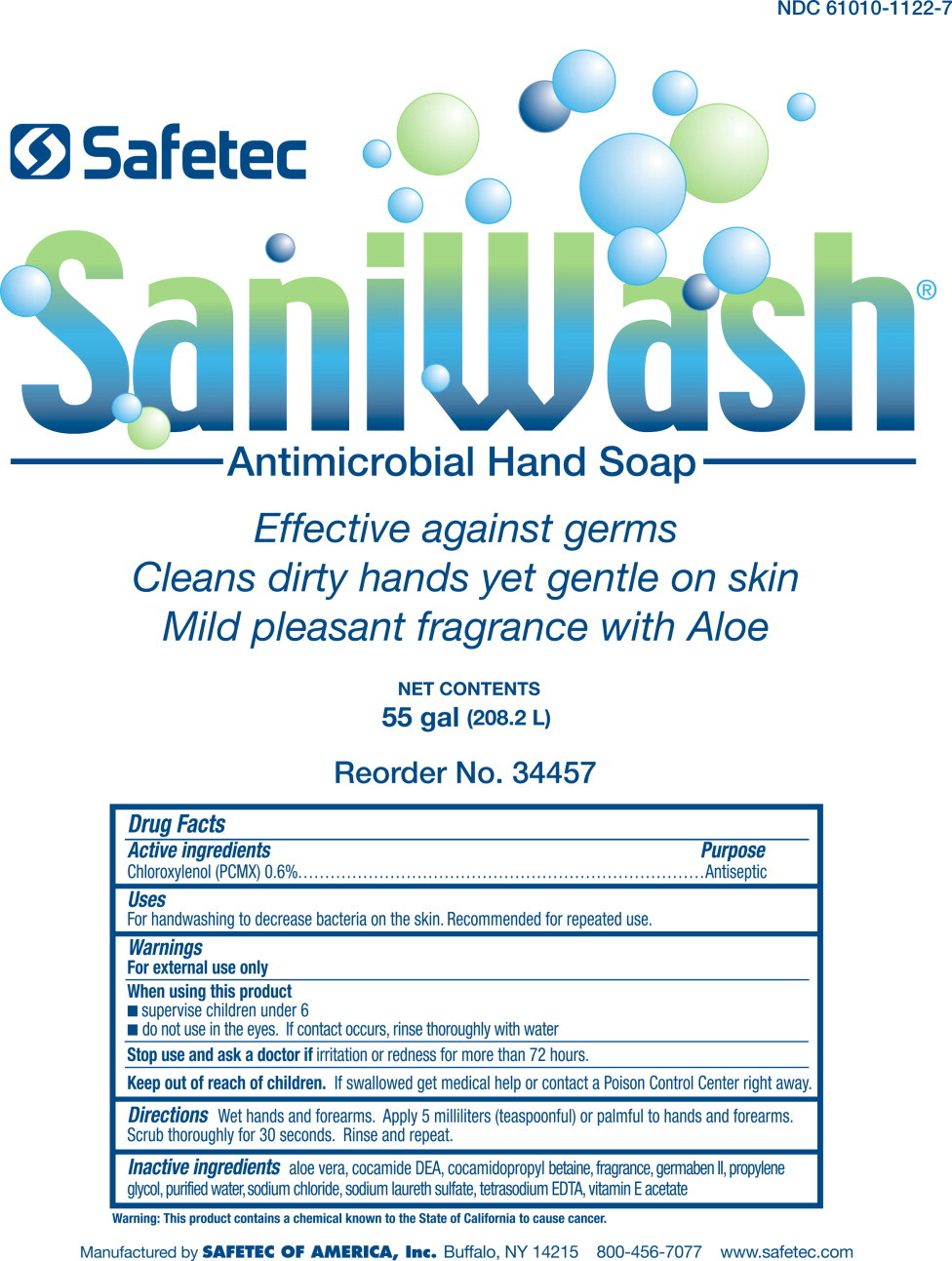 DRUG LABEL: Saniwash Antimicrobial
NDC: 61010-1122 | Form: LIQUID
Manufacturer: Safetec of America, Inc.
Category: otc | Type: HUMAN OTC DRUG LABEL
Date: 20240205

ACTIVE INGREDIENTS: CHLOROXYLENOL 0.006 mg/1 mL
INACTIVE INGREDIENTS: ALOE VERA LEAF; SODIUM LAURETH-3 SULFATE; COCO DIETHANOLAMIDE; COCAMIDOPROPYL BETAINE; PROPYLENE GLYCOL; PROPYLPARABEN; METHYLPARABEN; DIAZOLIDINYL UREA; WATER; SODIUM CHLORIDE; EDETATE SODIUM; .ALPHA.-TOCOPHEROL ACETATE

61010-1122, Saniwash

Drug Facts

Active ingredients

Chloroxylenol (PCMX) 0.6%

Purpose

Antiseptic

Uses

For handwashing to decrease bacteria on the skin. Recommended for repeated use.

Warnings

For external use only

When using this product

- supervise children under 6
- do not use in the eyes. If contact occurs, rinse thoroughly with water

Stop use and ask a doctor ifirritation or redness develop and persist for more than 72 hours.

Keep out of reach of children.If swallowed get medical help or contact a Poison Control Center right away.

Directions

Wet hands and forearms. Apply 5 milliliters (teaspoonful) or palmful to hands and forearms. Scrub thoroughly for 30 seconds. Rinse and repeat.

Inactive ingredients

aloe vera, cocamide DEA, cocamidopropyl betaine, fragrance, germaben II, propylene glycol, purified water, sodium chloride, sodium laureth sulfate, tetrasodium EDTA, vitamin E acetate

PRINCIPAL DISPLAY PANEL - 1 GALLON BOTTLE

NDC 61010-1122-6

Safetec

SaniWash

Antimicrobial Hand Soap

Effective against germs

Cleans dirty hands yet gentle on skin

Mild pleasant fragrance with Aloe

Reorder No. 34455

NET CONTENTS

1 gal (3.785 L)

PRINCIPAL DISPLAY PANEL - 800 mL Bag-In-Box

Manufactured by
Safetec

Safetec of America, Inc.

Buffalo, NY 14215

1-800-456-7077 www.safetec.com

Reorder No. 34465

NDC 61010-1122-4

27.05 fl. oz. (800 ml.)

SaniWash

Antimicrobial Hand Soap

PRINCIPAL DISPLAY PANEL - 16 oz. BOTTLE

NDC 61010-1122-3

SaniWash

Antimicrobial Hand Soap

Effective against germs

Cleans dirty hands yet gentle on skin

Mild pleasant fragrance with Aloe

NET CONTENTS

16 fl. oz. (473 ml)

Safetec

Reorder No. 34452

Principal Display Panel - Bottle Label

NDC 61010-1122-7

Safetec

SaniWash®

Antimicrobial Hand Soap

Effective against germs

Cleans dirty hands yet gentle on skin

Mild pleasant fragrance with Aloe

NET CONTENTS

55 gal (208.2 L)

Reorder No. 34457

Manufactured by SAFETEC OF AMERICA, Inc.Buffalo, NY 14215 800-456-7077 www.safetec.com